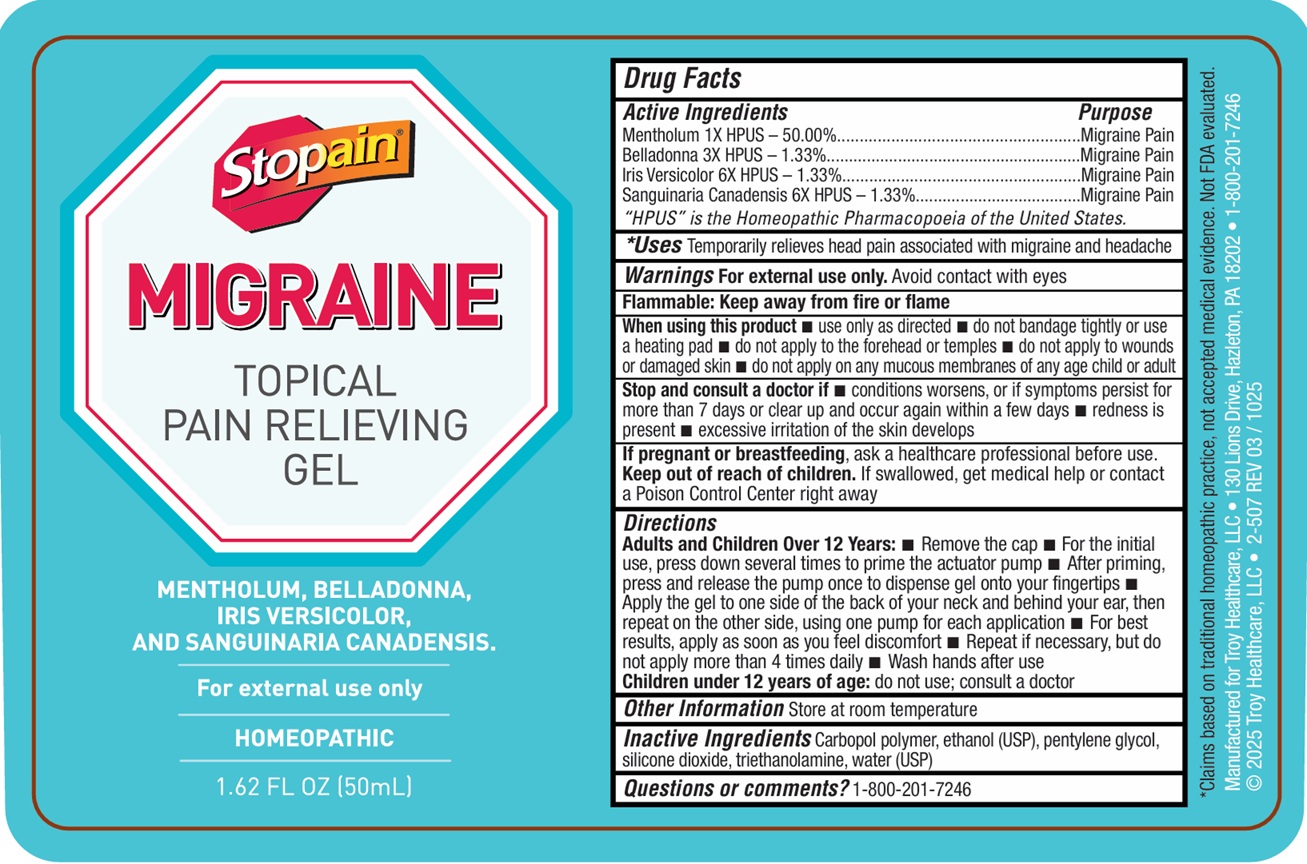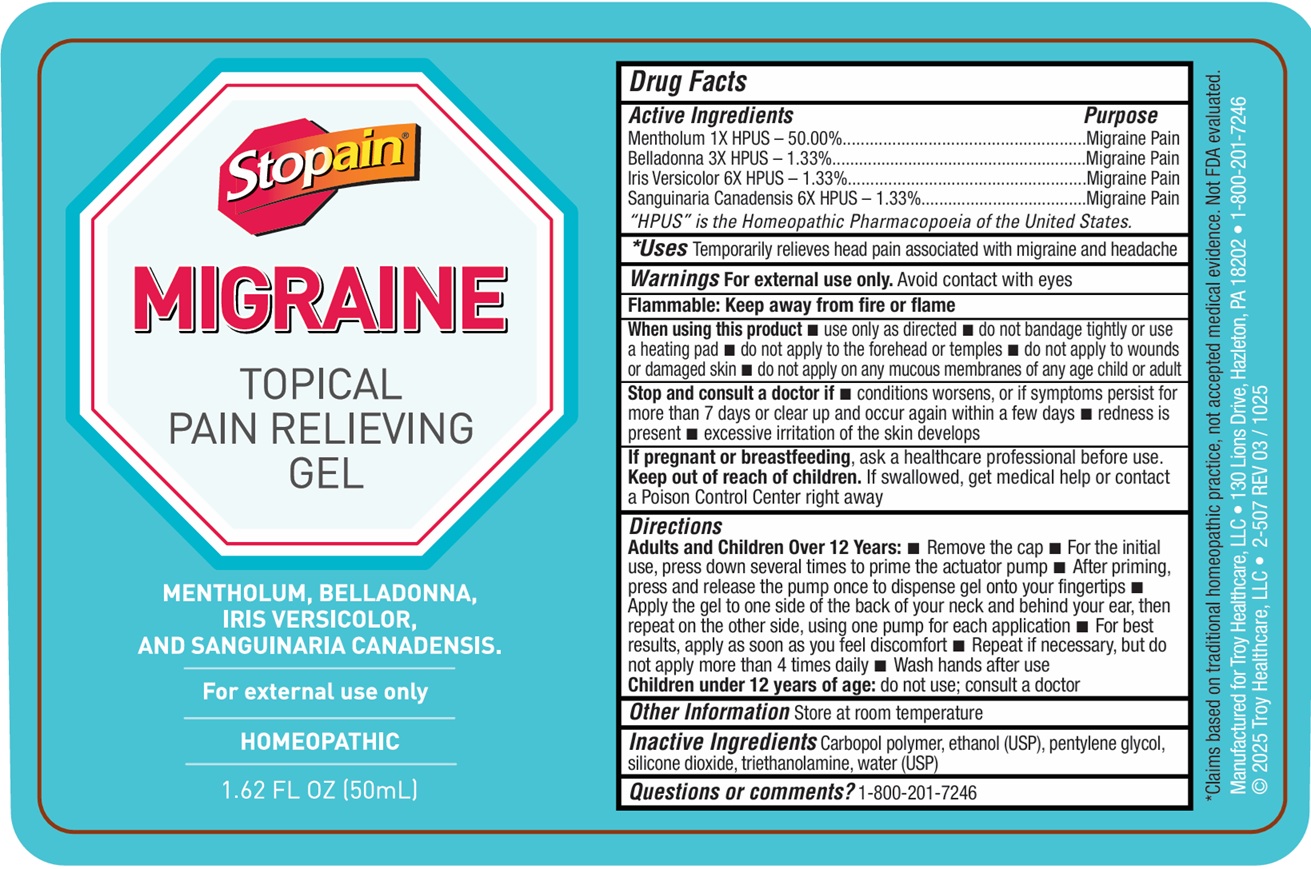 DRUG LABEL: Stopain Migraine Pain Relieving
NDC: 63936-8700 | Form: GEL
Manufacturer: TROY MANUFACTURING, INC
Category: homeopathic | Type: HUMAN OTC DRUG LABEL
Date: 20251124

ACTIVE INGREDIENTS: MENTHOL, UNSPECIFIED FORM 1 [hp_X]/50 mL; ATROPA BELLADONNA 3 [hp_X]/50 mL; IRIS VERSICOLOR ROOT 6 [hp_X]/50 mL; SANGUINARIA CANADENSIS ROOT 6 [hp_X]/50 mL
INACTIVE INGREDIENTS: ALCOHOL; PENTYLENE GLYCOL; SILICON DIOXIDE; TROLAMINE; WATER

Stopain Migraine Topical Pain Relieving Gel

Active Ingredients

Mentholum 1X HPUS-50.00%

Belladonna 3X HPUS-1.33%

Iris Versicolor 6X HPUS-1.33%

Sanguinaria Canadensis 6X HPUS-1.33%

Purpose

Migraine Pain

Uses

Provides temporary relief from migraine symptoms such as:

- Headaches
- Sensitivity to light
- nausea

Warnings

For external use only. Avoid contact with eyes.

Flammable: Keep away from fire or flame

When using this product

- use only as directed
- do not bandage tightly or use a heating pad
- do not apply to the forehead or temples
- do not apply to wounds or damaged skin

Stop and consult a doctor if

- condition worsens, or symptoms persist for more than 7 days or clear up and occur again within a few days
- redness or excessive irritation occurs

If pregnant or breast-feeding,

ask a healthcare professional before use.

Keep out of reach of children.

If swallowed, get medical help or contact a Poison Control Center right away.

Directions

Adults and children over 12 years:

Remove cap. For the initial use, press down several times to prime the actuator pump. After priming, press and release the pump once to dispense gel onto your fingertips. Apply the gel to one side of the back of your neck and behind your ear, then repeat on the other side, using one pump for each application. For optimal results, apply as soon as you experience discomfort. If symptoms persist after 30 minutes, you may reapply as needed, up to 4 times a day. Children under 12 years of age: do not use; consult a doctor.

Inactive Ingredients

Carbopol polymer, ethanol (USP), pentylene glycol, silicone dioxide, triethanolamine, water (USP)

Other Information

Store at room temperature.